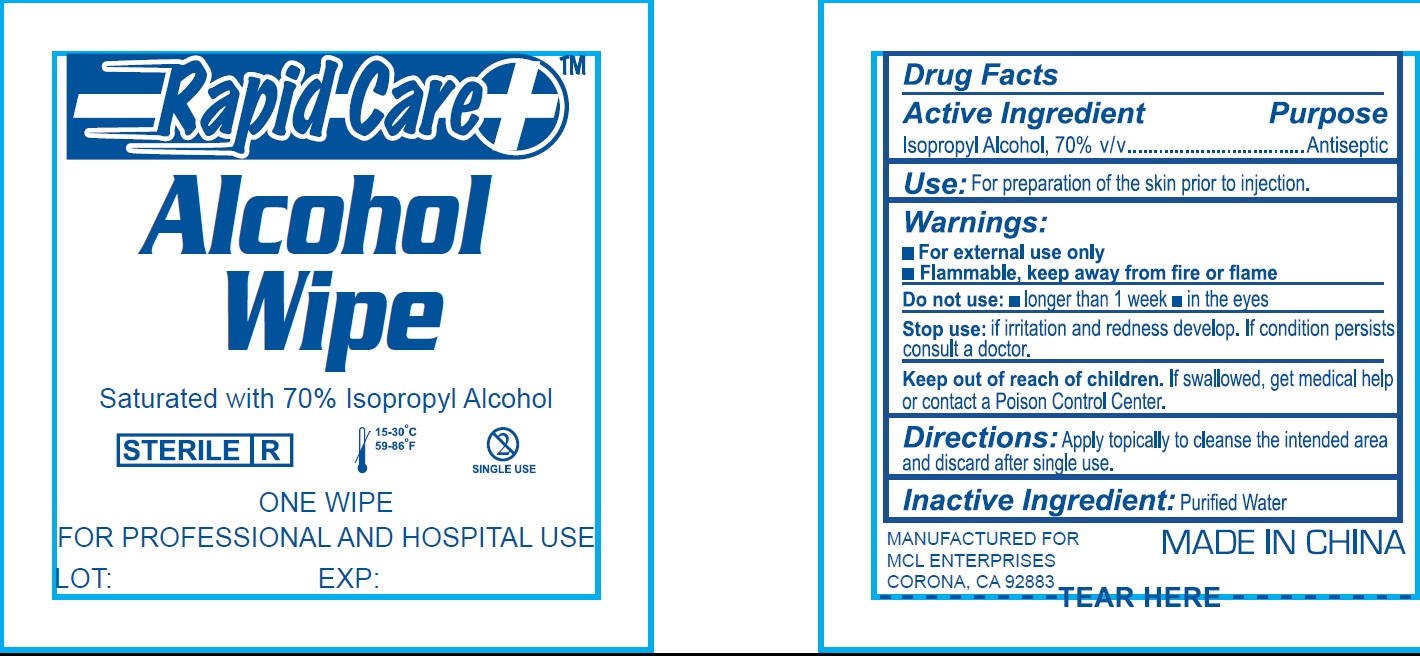 DRUG LABEL: Alcohol
NDC: 71622-004 | Form: PATCH
Manufacturer: MCL Enterprises
Category: otc | Type: HUMAN OTC DRUG LABEL
Date: 20170727

ACTIVE INGREDIENTS: ISOPROPYL ALCOHOL 700 mg/1 g
INACTIVE INGREDIENTS: WATER

Alcohol Wipe

Active Ingredient

Isopropyl Alcohol, 70% v/v

Purpose

Antiseptic

Use:

For preparation of the skin prior to injection.

Warnings:

- For external use only
- Flammable, keep away from fire or flame

Do not use:

- longer than 1 week
- in the eyes

Stop use:

- if irritation and redness develop. If condition persists consult a doctor.

Keep out of reach of children.

If swallowed, get medical help or contact a Poison Control Center.

Directions:

Apply topically to cleanse the intended area and discard after single use.

Inactive Ingredient:

Purified Water